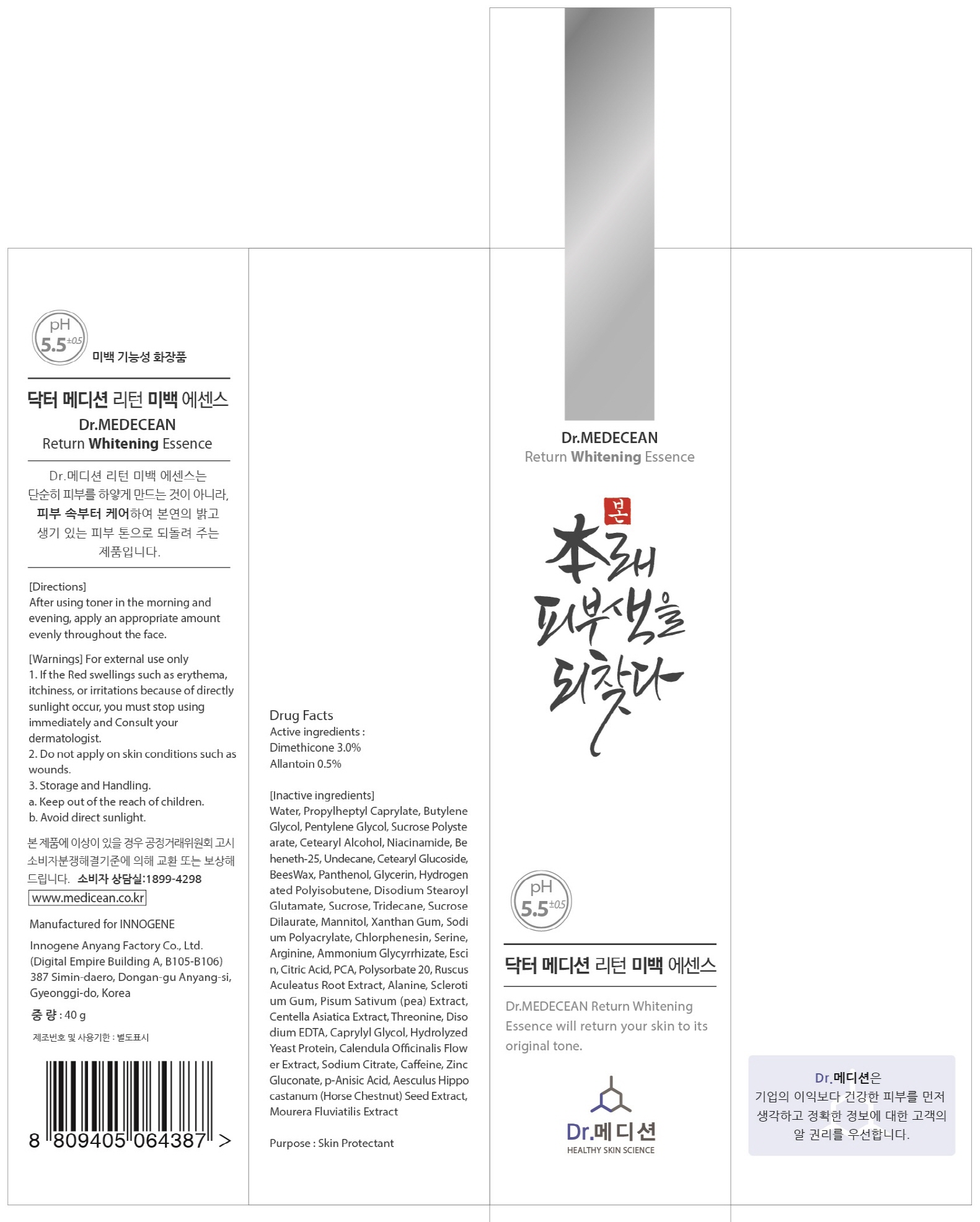 DRUG LABEL: Dr MEDECEAN Return Whitening Essence
NDC: 70540-050 | Form: LIQUID
Manufacturer: INNOGENE CO.,LTD
Category: otc | Type: HUMAN OTC DRUG LABEL
Date: 20170927

ACTIVE INGREDIENTS: Dimethicone 1.2 g/40 g; Allantoin 0.2 g/40 g
INACTIVE INGREDIENTS: WATER; BUTYLENE GLYCOL

ACTIVE INGREDIENT

Active ingredients: Dimethicone 3.0%, Allantoin 0.5%

INACTIVE INGREDIENT

Inactive ingredients: Water, Propylheptyl Caprylate, Butylene Glycol, Pentylene Glycol, Sucrose Polystearate, Cetearyl Alcohol, Niacinamide, Beheneth-25, Undecane, Cetearyl Glucoside, BeesWax, Panthenol, Glycerin, Hydrogenated Polyisobutene, Disodium Stearoyl Glutamate, Sucrose, Tridecane, Sucrose Dilaurate, Mannitol, Xanthan Gum, Sodium Polyacrylate, Chlorphenesin, Serine, Arginine, Ammonium Glycyrrhizate, Escin, Citric Acid, PCA, Polysorbate 20, Ruscus Aculeatus Root Extract, Alanine, Sclerotium Gum, Pisum Sativum (pea) Extract, Centella Asiatica Extract, Threonine, Disodium EDTA, Caprylyl Glycol, Hydrolyzed Yeast Protein, Calendula Officinalis Flower Extract, Sodium Citrate, Caffeine, Zinc Gluconate, p-Anisic Acid, Aesculus Hippocastanum (Horse Chestnut) Seed Extract, Mourera Fluviatilis Extract

PURPOSE

Purpose: Skin Protectant

WARNINGS

Warnings: For external use only

1. If the Red swellings such as erythema, itchiness, or irritations because of directly sunlight occur, you must stop using immediately and Consult your dermatologist. 2. Do not apply on skin conditions such as wounds. 3. Storage and Handling. a. Keep out of the reach of children. b. Avoid direct sunlight.

KEEP OUT OF REACH OF CHILDREN

Uses

Uses: Dr.MEDECEAN Return Whitening Essence will return your skin to its original tone.

Directions

Directions: After using toner in the morning and evening, apply an appropriate amount evenly throughout the face.